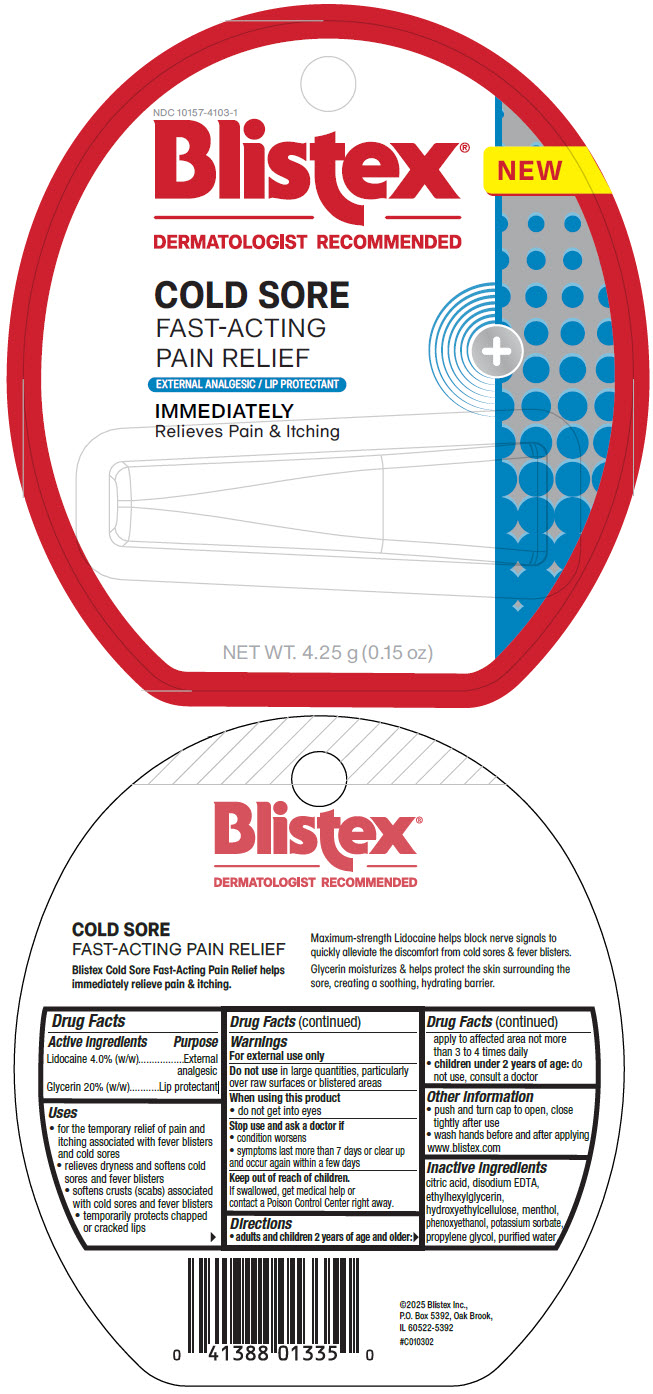 DRUG LABEL: Cold Sore Fast-Acting Pain Relief
NDC: 10157-4103 | Form: GEL
Manufacturer: Blistex Inc.
Category: otc | Type: HUMAN OTC DRUG LABEL
Date: 20250722

ACTIVE INGREDIENTS: GLYCERIN 200 mg/1 g; LIDOCAINE 40 mg/1 g
INACTIVE INGREDIENTS: WATER; PROPYLENE GLYCOL; CITRIC ACID MONOHYDRATE; HYDROXYETHYL CELLULOSE, UNSPECIFIED; PHENOXYETHANOL; ETHYLHEXYLGLYCERIN; POTASSIUM SORBATE; MENTHOL, UNSPECIFIED FORM; EDETATE DISODIUM

Cold Sore Fast-Acting Pain Relief

Drug Facts

ACTIVE INGREDIENT

Active ingredients | Purpose
Lidocaine 4.0% (w/w) | External analgesic
Glycerin 20% (w/w) | Lip protectant

Uses

- for the temporary relief of pain and itching associated with fever blisters and cold sores
- relieves dryness and softens cold sores and fever blisters
- softens crusts (scabs) associated with cold sores and fever blisters
- temporarily protects chapped or cracked lips

Warnings

For external use only

Do not use in large quantities, particularly over raw surfaces or blistered areas

When using this product

- do not get into eyes

Stop use and ask a doctor if

- condition worsens
- symptoms last more than 7 days or clear up and occur again within a few days

Keep out of reach of children.

If swallowed, get medical help or contact a Poison Control Center right away.

Directions

- adults and children 2 years of age and older: apply to affected area not more than 3 to 4 times daily
- children under 2 years of age: do not use, consult a doctor

Other information

- push and turn cap to open, close tightly after use
- wash hands before and after applying www.blistex.com

Inactive ingredients

citric acid, disodium EDTA, ethylhexylglycerin, hydroxyethylcellulose, menthol, phenoxyethanol, potassium sorbate, propylene glycol, purified water

PRINCIPAL DISPLAY PANEL - 4.25 g Tube Label

NDC 10157-4103-1

Blistex®
DERMATOLOGIST RECOMMENDED

NEW

COLD SORE

FAST-ACTING
PAIN RELIEF

EXTERNAL ANALGESIC / LIP PROTECTANT

IMMEDIATELY
Relieves Pain & Itching

NET WT. 4.25 g (0.15 oz)